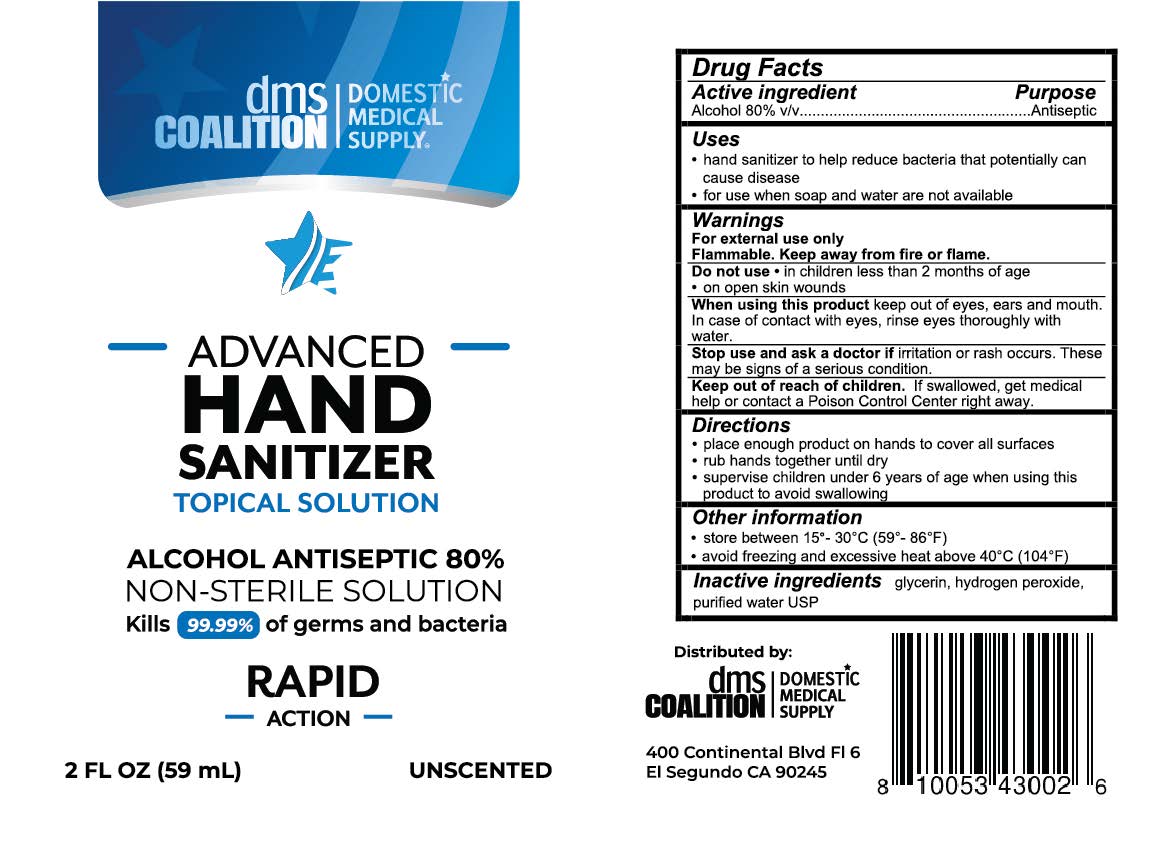 DRUG LABEL: DMS Coalition Hand Sanitizer
NDC: 79407-001 | Form: SOLUTION
Manufacturer: Domestic Medical Supply Coalition, LLC
Category: otc | Type: HUMAN OTC DRUG LABEL
Date: 20200701

ACTIVE INGREDIENTS: ALCOHOL 80 mL/100 mL
INACTIVE INGREDIENTS: HYDROGEN PEROXIDE; WATER; GLYCERIN

DMS Coalition Advanced Hand Sanitizer, Unscented

Drug Facts

Active ingredient

Alcohol 80% v/v

Purpose
Antiseptic

Uses

- hand sanitizer to help reduce bacteria that potentially can cause disease
- for use when soap and water are not available

Warnings
For external use only.
Flammable. Keep away from fire or flame.

Do not use

- in children less than 2 months of age
- on open skin wounds

When using this product keep out of eyes, ears and mouth. In case of contact with eyes, rinse eyes thoroughly with water.

Stop use and ask a doctor if irritation or rash occurs. These may be signs of a serious condition.

Keep out of reach of children. If swallowed, get medical help or contact a Poison Control Center immediately.

Directions

- place enough product on hands to cover all surfaces
- rub hands together until dry
- supervise children under 6 years of age when using this product to avoid swallowing

Other information

- store between 15-30°C (59-86°F)
- avoid freezing and excessive heat above 40“C (104°F)

Inactive ingredients

glycerin, hydrogen peroxide, purified water USP

Distributed by:
dms COALITION | DOMESTIC MEDICAL SUPPLY
400 Continental Blvd. Fl 6
El Segundo, CA 90245

PACKAGE LABEL

dms COALITION | DOMESTIC MEDICAL SUPPLY
ADVANCED HAND SANITIZER

TOPICAL SOLUTION
ALCOHOL ANTISEPTIC 80%
NON-STERILE SOLUTION

Kills 99.99% of germs and bacteria
RAPID ACTION
2 FL OZ (59 mL)
UNSCENTED